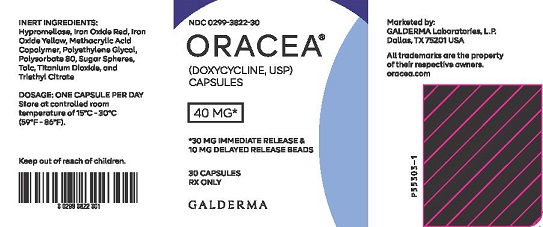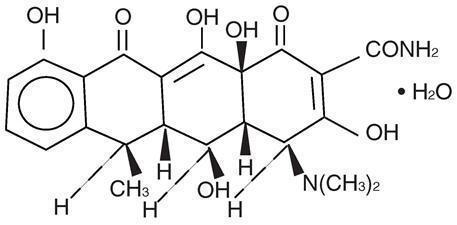 DRUG LABEL: ORACEA
NDC: 0299-3822 | Form: CAPSULE
Manufacturer: Galderma Laboratories, L.P.
Category: prescription | Type: HUMAN PRESCRIPTION DRUG LABEL
Date: 20250416

ACTIVE INGREDIENTS: DOXYCYCLINE 40 mg/1 1
INACTIVE INGREDIENTS: Hypromellose, Unspecified; Methacrylic Acid And Ethyl Acrylate Copolymer; Ferric Oxide Red; Ferric Oxide Yellow; Polyethylene Glycol, Unspecified; Polysorbate 80; Titanium Dioxide; Sucrose; Talc; Acetyl Triethylhexyl Citrate

HIGHLIGHTS OF PRESCRIBING INFORMATION

These highlights do not include all the information needed to use ORACEA® safely and effectively. See full prescribing information for ORACEA. ORACEA (doxycycline) capsules for oral use.
Initial U.S. Approval: 1967

1 INDICATIONS AND USAGE

ORACEA is a tetracycline-class drug indicated for the treatment of only inflammatory lesions (papules and pustules) of rosacea in adult patients. (1.1)

Limitations of Use
This formulation of doxycycline has not been evaluated in the treatment or prevention of infections. Do not use ORACEA for treating bacterial infections, providing antibacterial prophylaxis, or reducing the numbers or eliminating microorganisms associated with any bacterial disease. (1.2)
ORACEA has not been evaluated for the treatment of the erythematous, telangiectatic, or ocular components of rosacea. (1.2)

2 DOSAGE AND ADMINISTRATION

Take one ORACEA capsule (40 mg) once daily in the morning on an empty stomach, preferably at least one hour prior to or two hours after meals. (2.1)
Exceeding the recommended dosage may result in an increased incidence of side effects including the development of resistant microorganisms. (2.2, 5.9)

3 DOSAGE FORMS AND STRENGTHS

40 mg capsule. (3)

4 CONTRAINDICATIONS

ORACEA is contraindicated in persons who have shown hypersensitivity to doxycycline or other tetracyclines. (4)

5 WARNINGS AND PRECAUTIONS

- The use of ORACEA during tooth development (the second and third trimesters of pregnancy, infancy and childhood up to the age of 8 years) may cause permanent discoloration of the teeth (yellow-gray-brown) and reversible inhibition of bone growth. (5.1, 5.2, 8.1, 8.4)
- Treatment with antibacterial agents alters the normal flora of the colon leading to overgrowth of Clostridium difficile. If C. difficile associated diarrhea occurs, discontinue ORACEA. (5.3)
- If renal impairment exists, ORACEA doses may need to be adjusted to avoid excessive systemic accumulations of the drug and possible liver injury. (5.4)
- Photosensitivity can occur with ORACEA; Patients should minimize or avoid exposure to natural or artificial sunlight. (5.5)
- Tetracyclines have been associated with the development of autoimmune syndromes; if symptoms develop, discontinue ORACEA immediately. (5.6)
- ORACEA may cause pseudotumor cerebri (benign intracranial hypertension). Discontinue ORACEA if symptoms occur. (5.8)
- Bacterial resistance to tetracyclines may develop in patients using ORACEA. It should only be used as indicated. (5.9)

6 ADVERSE REACTIONS

Some of the most common adverse reactions (incidence >2% and more common than with placebo) are nasopharyngitis, sinusitis, diarrhea, hypertension and aspartate aminotransferase increase. (6)
To report SUSPECTED ADVERSE REACTIONS, contact Galderma Laboratories, L.P. at 1-866-735-4137 or FDA at 1-800-FDA-1088 or www.fda.gov/medwatch.

7 DRUG INTERACTIONS

- Patients on anticoagulant therapy may require downward adjustment of their anticoagulant dosage. (7.1)
- Some bacteriostatic drugs may interfere with the bactericidal action of penicillin, it is advisable to avoid giving tetracycline-class drugs in conjunction with penicillin. (7.2)
- The concurrent use of tetracycline and methoxyflurane has been reported to result in fatal renal toxicity. (7.3)

8 USE IN SPECIFIC POPULATIONS

Lactation: Breastfeeding is not recommended (8.2)

FULL PRESCRIBING INFORMATION

1 INDICATIONS AND USAGE

1.1 Indication

ORACEA is indicated for the treatment of only inflammatory lesions (papules and pustules) of rosacea in adult patients. No meaningful effect was demonstrated for generalized erythema (redness) of rosacea.

1.2 Limitations of Use

This formulation of doxycycline has not been evaluated in the treatment or prevention of infections. Do not use ORACEA for treating bacterial infections, providing antibacterial prophylaxis, or reducing the numbers or eliminating microorganisms associated with any bacterial disease. To reduce the development of drug-resistant bacteria as well as to maintain the effectiveness of other antibacterial drugs, ORACEA should be used only as indicated.

ORACEA has not been evaluated for the treatment of the erythematous, telangiectatic, or ocular components of rosacea.

2 DOSAGE AND ADMINISTRATION

2.1 General Dosing Information

Take one ORACEA capsule (40 mg) once daily in the morning on an empty stomach, preferably at least one hour prior to or two hours after meals. Administration of adequate amounts of fluid along with the capsules is recommended to wash down the capsule to reduce the risk of esophageal irritation and ulceration [see Adverse Reactions (6)].

2.2 Important Considerations for Dosing Regimen

The dosage of ORACEA differs from that of doxycycline used to treat infections. Exceeding the recommended dosage may result in an increased incidence of side effects including the development of resistant organisms.

3 DOSAGE FORMS AND STRENGTHS

40 mg beige opaque capsule imprinted with “GLD 40”

4 CONTRAINDICATIONS

This drug is contraindicated in persons who have shown hypersensitivity to doxycycline or any of the other tetracyclines.

5 WARNINGS AND PRECAUTIONS

5.1 Inhibition of Bone Growth During Fetal and Pediatric Development

Doxycycline, like other tetracycline-class drugs, may cause inhibition of bone growth when administered during the second and third trimesters of pregnancy, infancy, and childhood. All tetracyclines form a stable calcium complex in any bone-forming tissue. A decrease in fibula growth rate has been observed in premature human infants given oral tetracycline in doses of 25 mg/kg every 6 hours. This reaction was shown to be reversible when the drug was discontinued. If doxycycline is used during the second or third trimester of pregnancy, advise the patient of the potential risk to the fetus [see Use in Specific Populations (8.1)].

5.2 Tooth Discoloration During Fetal and Pediatric Development

The use of tetracycline class drugs orally during tooth development (last half of pregnancy, infancy, and childhood up to the age of 8 years) may cause permanent discoloration of the teeth (yellow-gray-brown). This adverse reaction is more common during long-term use of the drug but has been observed following repeated short-term courses. Enamel hypoplasia has also been reported. Use of tetracycline drugs is not recommended during tooth development [see Use in Specific Populations (8.1)].

5.3 Clostridium difficile Associated Diarrhea (CDAD)

Clostridium difficile associated diarrhea (CDAD) has been reported with nearly all antibacterial agents, including doxycycline, and may range in severity from mild diarrhea to fatal colitis. Treatment with antibacterial agents alters the normal flora of the colon leading to overgrowth of C. difficile.
C. difficile produces toxins A and B which contribute to the development of CDAD. Hypertoxin producing strains of C. difficile cause increased morbidity and mortality, as these infections can be refractory to antimicrobial therapy and may require colectomy. CDAD must be considered in all patients who present with diarrhea following antibiotic use. Careful medical history is necessary since CDAD has been reported to occur over two months after the administration of antibacterial agents.
If CDAD is suspected or confirmed, ongoing antibiotic use not directed against C. difficile may need to be discontinued. Appropriate management should be instituted as clinically indicated.

5.4 Metabolic Effects

The anti-anabolic action of the tetracyclines may cause an increase in BUN. While this is not a problem in those with normal renal function, in patients with significantly impaired function, higher serum levels of tetracycline-class antibiotics may lead to azotemia, hyperphosphatemia, and acidosis. If renal impairment exists, even usual oral or parenteral doses may lead to excessive systemic accumulations of the drug and possible liver toxicity. Under such conditions, lower than usual total doses are indicated, and if therapy is prolonged, serum level determinations of the drug may be advisable.

5.5 Photosensitivity

Photosensitivity manifested by an exaggerated sunburn reaction has been observed in some individuals taking tetracyclines. Although this was not observed during the duration of the clinical studies with ORACEA, patients should minimize or avoid exposure to natural or artificial sunlight (tanning beds or UVA/B treatment) while using ORACEA. If patients need to be outdoors while using ORACEA, they should wear loose-fitting clothes that protect skin from sun exposure and discuss other sun protection measures with their physician.

5.6 Autoimmune Syndromes

Tetracyclines have been associated with the development of autoimmune syndromes. Symptoms may be manifested by fever, rash, arthralgia, and malaise. In symptomatic patients, liver function tests, ANA, CBC, and other appropriate tests should be performed to evaluate the patients. Use of all tetracycline-class drugs should be discontinued immediately.

5.7 Tissue Hyperpigmentation

Tetracycline-class drugs are known to cause hyperpigmentation. Tetracycline therapy may induce hyperpigmentation in many organs, including nails, bone, skin, eyes, thyroid, visceral tissue, oral cavity (teeth, mucosa, alveolar bone), sclerae and heart valves. Skin and oral pigmentation has been reported to occur independently of time or amount of drug administration, whereas other pigmentation has been reported to occur upon prolonged administration. Skin pigmentation includes diffuse pigmentation as well as over sites of scars or injury.

5.8 Pseudotumor Cerebri

Pseudotumor cerebri (benign intracranial hypertension) in adults has been associated with the use of tetracyclines. The usual clinical manifestations are headache and blurred vision. Bulging fontanels have been associated with the use of tetracyclines in infants. While both of these conditions and related symptoms usually resolve after discontinuation of the tetracycline, the possibility for permanent sequelae exists. Patients should be questioned for visual disturbances prior to initiation of treatment with tetracyclines and should be routinely checked for papiledema while on treatment.

5.9 Development of Drug Resistant Bacteria

Bacterial resistance to tetracyclines may develop in patients using ORACEA. Because of the potential for drug-resistant bacteria to develop during the use of ORACEA, it should only be used as indicated.

5.10 Superinfection

As with other antibiotic preparations, use of ORACEA may result in overgrowth of non-susceptible microorganisms, including fungi. If superinfection occurs, ORACEA should be discontinued and appropriate therapy instituted. Although not observed in clinical trials with ORACEA, the use of tetracyclines may increase the incidence of vaginal candidiasis. ORACEA should be used with caution in patients with a history of or predisposition to Candida overgrowth.

5.11 Laboratory Monitoring

Periodic laboratory evaluations of organ systems, including hematopoietic, renal and hepatic studies should be performed. Appropriate tests for autoimmune syndromes should be performed as indicated.

5.12 Fixed Drug Eruptions

Fixed drug eruptions have occurred with doxycycline and have been associated with worsening severity upon subsequent administrations, including generalized bullous fixed drug eruption [see Adverse Reactions (6.2)]. If severe reactions occur, discontinue ORACEA immediately and initiate appropriate therapy.

6 ADVERSE REACTIONS

6.1 Clinical Trials Experience

Because clinical trials are conducted under widely varying conditions, adverse reaction rates observed in the clinical trials of a drug cannot be directly compared to rates in the clinical trials of another drug and may not reflect the rates observed in practice.

Adverse Reactions in Clinical Trials of ORACEA: In controlled clinical trials of adult subjects with mild to moderate rosacea, 537 subjects received ORACEA or placebo over a 16-week period. The following table summarizes selected adverse reactions that occurred in the clinical trials at a rate of ≥1% for the active arm:

Table 1. Incidence (%) of Selected Adverse Reactions in Clinical Trials of ORACEA (n=269) v.s. Placebo (n=268)
 | ORACEA | Placebo
Nasopharyngitis | 13 (5) | 9 (3)
Pharyngolaryngeal Pain | 3 (1) | 2 (1)
Sinusitis | 7 (3) | 2 (1)
Nasal Congestion | 4 (2) | 2 (1)
Fungal Infection | 5 (2) | 1 (0)
Influenza | 5 (2) | 3 (1)
Diarrhea | 12 (5) | 7 (3)
Abdominal Pain Upper | 5 (2) | 1 (0)
Abdominal Distention | 3 (1) | 1 (0)
Abdominal Pain | 3 (1) | 1 (0)
Stomach Discomfort | 3 (1) | 2 (1)
Dry Mouth | 3 (1) | 0 (0)
Hypertension | 8 (3) | 2 (1)
Blood Pressure Increase | 4 (2) | 1 (0)
Aspartate Aminotransferase Increase | 6 (2) | 2 (1)
Blood Lactate Dehydrogenase Increase | 4 (2) | 1 (0)
Blood Glucose Increase | 3 (1) | 0 (0)
Anxiety | 4 (2) | 0 (0)
Pain | 4 (2) | 1 (0)
Back Pain | 3 (1) | 0 (0)
Sinus Headache | 3 (1) | 0 (0)
Note: Percentages based on total number of study participants in each treatment group.

Adverse Reactions for Tetracyclines: The following adverse reactions have been observed in patients receiving tetracyclines at higher, antimicrobial doses:

Gastrointestinal: anorexia, nausea, vomiting, diarrhea, glossitis, dysphagia, enterocolitis, and inflammatory lesions (with vaginal candidiasis) in the anogenital region. Hepatotoxicity, Esophagitis and esophageal ulcerations have been reported in patients receiving the capsule forms of the drugs in the tetracycline-class. Most of the patients experiencing esophagitis and/or esophageal ulceration took their medication immediately before lying down [see Dosage and Administration (2)].
Renal toxicity: Rise in BUN has been reported and is apparently dose-related [see Warnings and Precautions (5.4)].
Skin: maculopapular and erythematous rashes. Exfoliative dermatitis. Photosensitivity is discussed above [see Warnings and Precautions (5.5)].
Hypersensitivity reactions: urticaria, angioneurotic edema, anaphylaxis, anaphylactoid purpura, serum sickness, pericarditis, and exacerbation of systemic lupus erythematosus.
Blood: Hemolytic anemia, thrombocytopenia, neutropenia, and eosinophilia.

6.2 Postmarketing Adverse Reactions

Because these reactions are reported voluntarily from a population of uncertain size, it is not always possible to reliably estimate their frequency or establish a causal relationship to drug exposure. The following adverse reactions have been identified during post approval use of ORACEA.
Nervous system: Pseudotumor cerebri (benign intracranial hypertension), headache.
Skin: fixed drug eruption
Psychiatric: depression, anxiety, suicidal ideation, insomnia, abnormal dreams, hallucination

7 DRUG INTERACTIONS

7.1 Anticoagulants

Because tetracyclines have been shown to depress plasma prothrombin activity, patients who are on anticoagulant therapy may require downward adjustment of their anticoagulant dosage.

7.2 Penicillin

Since bacteriostatic drugs may interfere with the bactericidal action of penicillin, it is advisable to avoid giving tetracycline-class drugs in conjunction with penicillin.

7.3 Methoxyflurane

The concurrent use of tetracycline and methoxyflurane has been reported to result in fatal renal toxicity.

7.4 Antacids and Iron Preparations

Absorption of tetracyclines is impaired by bismuth subsalicylate, proton pump inhibitors, antacids containing aluminum, calcium or magnesium and iron-containing preparations.

7.5 Oral Retinoids

There have been reports of pseudotumor cerebri (benign intracranial hypertension) associated with the concomitant use of isotretinoin and tetracyclines. Since both oral retinoids, including isotretinoin and acitretin, and the tetracyclines, primarily minocycline, can cause increased intracranial pressure, the concurrent use of an oral retinoid and a tetracycline should be avoided.

7.6 Barbiturates and Anti-epileptics

Barbiturates, carbamazepine, and phenytoin decrease the half-life of doxycycline.

7.7 Drug/Laboratory Test Interactions

False elevations of urinary catecholamine levels may occur due to interference with the fluorescence test.

8 USE IN SPECIFIC POPULATIONS

8.1 Pregnancy

Risk Summary
Doxycycline may cause reversible inhibition of bone growth and permanent discoloration of deciduous teeth when administered during the second and third trimesters of pregnancy [see Warnings and Precautions (5.1 and 5.2)]. Available data from published studies have not shown a difference in major birth defect risk with doxycycline exposure in the first trimester of pregnancy compared to unexposed pregnancies. Avoid use of ORECEA during the second and third trimester of pregnancy.
The background risk of major birth defects and miscarriage for the indicated population is unknown. All pregnancies have a background risk of birth defect, loss, or other adverse outcomes. In the U.S. general population, the estimated background risk of major birth defects and miscarriage in clinically recognized pregnancies is 2–4% and 15–20%, respectively.
Data
Human Data
Published studies, including epidemiological and observational studies, with use of doxycycline during the first trimester of pregnancy have not identified drug-related increases in major birth defects.
The use of tetracycline during tooth development (second and third trimester of pregnancy) may cause permanent discoloration of deciduous teeth (yellow-gray-brown). This adverse reaction is more common during long-term use of the drug but has been observed following repeated short- term courses.
Animal Data
Results from animal studies indicate that doxycycline crosses the placenta and is found in fetal tissues.

8.2 Lactation

Risk Summary
Based on available published data, doxycycline is likely to be present in human breast milk but the specific concentration in breastmilk is not clear. There is no information on the effects of doxycycline on the breastfed infant or the effects on milk production. Because there are other antibacterial drug options available to treat rosacea in lactating women and because of the potential for serious adverse reactions, including tooth discoloration and inhibition of bone growth, advise patients that breastfeeding is not recommended during treatment with ORACEA and for 5 days after the last dose.

8.4 Pediatric Use

ORACEA should not be used in infants and children less than 8 years of age [see Warnings and Precautions (5.1)]. ORACEA has not been studied in children of any age with regard to safety or efficacy, therefore use in children is not recommended.

8.5 Geriatric Use

Clinical studies of ORACEA did not include sufficient numbers of subjects aged 65 and over to determine whether they respond differently from younger subjects. Other reported clinical experience has not identified differences in responses between elderly and younger patients. In general, dose selection for an elderly patient should be cautious, usually starting at the low end of the dosing range, reflecting the greater frequency of decreased hepatic, renal, or cardiac function, and concomitant disease or other drug therapy.

11 DESCRIPTION

ORACEA (doxycycline, USP) Capsules 40 mg are hard gelatin capsule shells filled with two types of doxycycline beads (30 mg immediate release and 10 mg delayed release) that together provide a dose of 40 mg of anhydrous doxycycline (C22H24N2O8).

The structural formula of doxycycline, USP is:

with an empirical formula of C22H24N2O8•H2O and a molecular weight of 462.46. The chemical designation for doxycycline is 2-Naphthacenecar-boxamide,4-(dimethylamino)-1,4,4a,5,5a,6,11,12a-octahydro-3,5,10,12,12a-pentahydroxy-6-methyl-1,11-dioxo-, [4S-(4α, 4aα, 5α, 5aα, 6α,12aα)]-, monohydrate. It is very slightly soluble in water.

Inert ingredients in the formulation are: hypromellose, iron oxide red, iron oxide yellow, methacrylic acid copolymer, polyethylene glycol, Polysorbate 80, sugar spheres, talc, titanium dioxide, and triethyl citrate.

12 CLINICAL PHARMACOLOGY

12.1 Mechanism of Action

The mechanism of action of ORACEA in the treatment of inflammatory lesions of rosacea is unknown.

12.3 Pharmacokinetics

ORACEA capsules are not bioequivalent to other doxycycline products. The pharmacokinetics of doxycycline following oral administration of
ORACEA was investigated in 2 volunteer studies involving 61 adults. Pharmacokinetic parameters for ORACEA following single oral doses and at steady-state in healthy subjects are presented in Table 2.

Table 2. Pharmcokinetic Parameters [Mean (± SD)] for ORACEA
 | N | Cmax [Mean] (ng/mL) | Tmax [Median] (hr) | AU0-∞ (ng●hr/mL) | t½ (hr)
Single Dose 40 mg capsules | 30 | 510 ± 220.7 | 3.00 (1.0 - 4.1) | 9227 ± 3212.8 | 21.2 ± 7.6
Steady-State [Day 7] 40 mg capsules | 31 | 600 ± 194.2 | 2.00 (1.0 - 4.0) | 7543 ± 2443.9 | 23.2 ± 6.2

Absorption: In a single-dose food-effect study involving administration of ORACEA to healthy volunteers, concomitant administration with a 1000 calorie, high-fat, high-protein meal that included dairy products, resulted in a decrease in the rate and extent of absorption (Cmax and AUC) by about 45% and 22%, respectively, compared to dosing under fasted conditions. This decrease in systemic exposure can be clinically significant, and therefore if ORACEA is taken close to meal times, it is recommended that it be taken at least one hour prior to or two hours after meals.

Distribution: Doxycycline is greater than 90% bound to plasma proteins.

Metabolism: Major metabolites of doxycycline have not been identified. However, enzyme inducers such as barbiturates, carbamazepine, and phenytoin decrease the half-life of doxycycline.

Excretion: Doxycycline is excreted in the urine and feces as unchanged drug. It is reported that between 29% and 55.4% of an administered dose can be accounted for in the urine by 72 hours. Terminal half-life averaged 21.2 hours in subjects receiving a single dose of ORACEA.

Special Populations

Geriatric: Doxycycline pharmacokinetics have not been evaluated in geriatric patients.

Pediatric: Doxycycline pharmacokinetics have not been evaluated in pediatric patients [see Warnings and Precautions (5.1)]

Gender: The pharmacokinetics of ORACEA were compared in 16 male and 14 female subjects under fed and fasted conditions. While female subjects had a higher Cmax and AUC than male subjects, these differences were thought to be due to differences in body weight/lean body mass.

Race: Differences in doxycycline pharmacokinetics among racial groups have not been evaluated.

Renal Insufficiency: Studies have shown no significant difference in serum half-life of doxycycline in patients with normal and severely impaired renal function. Hemodialysis does not alter the serum half-life of doxycycline.

Hepatic Insufficiency: Doxycycline pharmacokinetics have not been evaluated in patients with hepatic insufficiency.

Gastric Insufficiency:In a study in healthy volunteers (N=24) the bioavailability of doxycycline is reported to be reduced at high pH. This reduced bioavailability may be clinically significant in patients with gastrectomy, gastric bypass surgery or who are otherwise deemed achlorhydric.

Drug Interactions: [see Drug Interactions (7)].

12.4 Microbiology

Doxycycline is a member of the tetracycline-class of drugs. The plasma concentrations of doxycycline achieved with ORACEA during administration [see Clinical Pharmacology (12.3) and Dosage and Administration (2.2)] are less than the concentration required to treat bacterial diseases. ORACEA should not be used for treating bacterial infections, providing antibacterial prophylaxis, or reducing the numbers or eliminating microorganisms associated with any bacterial disease [see Indications and Usage (1.2)]. In vivo microbiological studies utilizing a similar drug exposure for up to 18 months demonstrated no detectable long term effects on bacterial flora of the oral cavity, skin, intestinal tract and vagina.

13 NONCLINICAL TOXICOLOGY

13.1 Carcinogenesis, Mutagenesis, Impairment of Fertility

Doxycycline was assessed for potential to induce carcinogenesis in a study in which the compound was administered to Sprague-Dawley rats by gavage at dosages of 20, 75, and 200 mg/kg/day for two years. An increased incidence of uterine polyps was observed in female rats that received 200 mg/kg/day, a dosage that resulted in a systemic exposure to doxycycline approximately 12.2 times that observed in female humans who use ORACEA [exposure comparison based upon area under the curve (AUC) values]. No impact upon tumor incidence was observed in male rats up to at 200 mg/kg/day, or in females at the lower dosages studied.

Doxycyline was assessed for potential to induce carcinogenesis in CD-1 mice by gavage at dosages 20, 75, and 150 mg/kg/day in males and at dosages of 20, 100, and 300 mg/kg/day in females. No impact upon tumor incidence was observed in male and female mice at systemic exposures approximately 4.2 and 8.3 times that observed in humans, respectively.

Doxycycline demonstrated no potential to cause genetic toxicity in an in vitro point mutation study with mammalian cells (CHO/HGPRT forward mutation assay) or in an in vivo micronucleus assay conducted in CD-1 mice. However, data from an in vitro mammalian chromosomal aberration assay conducted with CHO cells suggest that doxycycline is a weak clastogen. Oral administration of doxycycline to male and female Sprague-Dawley rats adversely affected fertility and reproductive performance, as evidenced by increased time for mating to occur, reduced sperm motility, velocity, and concentration, abnormal sperm morphology, and increased pre-and post-implantation losses. Doxycycline induced reproductive toxicity at all dosages that were examined in this study, as even the lowest dosage tested (50 mg/kg/day) induced a statistically significant reduction in sperm velocity. Note that 50 mg/kg/day is approximately 3.6 times the amount of doxycycline contained in the recommended daily dose of ORACEA when compared on the basis of AUC estimates. Although doxycycline impairs the fertility of rats when administered at sufficient dosage, the effect of ORACEA on human fertility is unknown.

14 CLINICAL STUDIES

The safety and efficacy of ORACEA in the treatment of only inflammatory lesions (papules and pustules) of rosacea was evaluated in two randomized, placebo-controlled, multi-centered, double-blind, 16-week Phase 3 trials involving 537 subjects (total of 269 subjects on ORACEA from the two trials) with rosacea (10 to 40 papules and pustules and two or fewer nodules). Mean baseline lesion counts were 20 and 21 for ORACEA and placebo subject groups respectively. Pregnant and nursing women, subjects <18 years of age, and subjects with ocular rosacea and/or blepharitis/meibomianitis who require ophthalmologic treatment were excluded from trials.

At Week 16, subjects in the ORACEA group were evaluated using co-primary endpoints of mean reduction in lesion counts and a dichotomized static Investigator’s Global Assessment of Clear or Almost Clear (defined as 1 to 2 small papules or pustules) when compared to the placebo group in both Phase 3 trials.

Table 3: Clinical Results of ORACEA versus Placebo
 | Study 1 |  | Study 2
 | ORACEA | Placebo | ORACEA | Placebo
 | 40 mg N=127 | N=124 | 40 mg N=142 | N=144
Mean Change in Lesion Count from Baseline | - 11.8 | - 5.9 | - 9.5 | - 4.3
No. (%) of Subjects Clear or Almost Clear in the IGA [Investigator's Global Assessment] | 39 (30.7%) | 24 (19.4%) | 21 (14.8%) | 9 (6.3%)

Subjects treated with ORACEA did not demonstrate significant improvement in erythema when compared to those treated with placebo.

16 HOW SUPPLIED/STORAGE AND HANDLING

ORACEA (beige opaque capsule imprinted with “GLD 40”) containing doxycycline, USP in an amount equivalent to 40 mg of anhydrous doxycycline.

Bottle of 30 (NDC 0299-3822-30).

Storage:

All products are to be stored at controlled room temperatures of 59°F - 86°F (15°C - 30°C) and dispensed in tight, light-resistant containers (USP).

Keep out of reach of children.

17 PATIENT COUNSELING INFORMATION

See FDA-approved patient labeling (Patient Information)

Patients taking ORACEA Capsules 40 mg should receive the following information and instructions:

- Advise pregnant women that doxycycline, like other tetracycline-class drugs, may cause permanent discoloration of deciduous teeth and reversible inhibition of bone growth when administered during the second and third trimesters of pregnancy [see Warnings and Precautions (5.1 and 5.2) and Use in Specific Populations (8.1)].
- Advise women not to breastfeed during treatment with ORACEA and for 5 days after the last dose [see Use in Specific Populations (8.2)].
- Advise patients that use of tetracycline class drugs orally during tooth development (infancy and childhood up to the age of 8 years) may cause permanent discoloration of the teeth (yellow-gray-brown).
- Advise patients that use of doxycycline, like other tetracycline-class drugs, may cause inhibition of bone growth when administered during infancy and childhood.
- Advise patients that pseudomembranous colitis can occur with doxycycline therapy. If patients develop watery or bloody stools, they should seek medical attention.
- Advise patients that pseudotumor cerebri can occur with doxycycline therapy. If patients experience headache or blurred vision they should seek medical attention.
- Photosensitivity manifested by an exaggerated sunburn reaction has been observed in some individuals taking tetracyclines, including doxycycline. Patients should minimize or avoid exposure to natural or artificial sunlight (tanning beds or UVA/B treatment) while using doxycycline. If patients need to be outdoors while using doxycycline, they should wear loose-fitting clothes that protect skin from sun exposure and discuss other sun protection measures with their physician. Treatment should be discontinued at the first evidence of sunburn.
- Autoimmune syndromes, including drug-induced lupus-like syndrome, autoimmune hepatitis, vasculitis and serum sickness have been observed with tetracycline-class drugs, including doxycycline. Symptoms may be manifested by arthralgia, fever, rash and malaise. Patients who experience such symptoms should be cautioned to stop the drug immediately and seek medical help.
- Counsel patients about discoloration of skin, scars, teeth or gums that can arise from doxycycline therapy.
- Advise patients to take ORACEA exactly as directed. Increasing doses beyond 40 mg every morning may increase the likelihood that bacteria will develop resistance and will not be treatable by other antibacterial drugs in the future.

PATIENT INFORMATION

ORACEA (Or-RAY-sha)
(doxycycline) capsules

Read this Patient Information before you start taking ORACEA and each time you get a refill. There may be new information. This information does not take the place of talking to your doctor about your medical condition or treatment.

What is ORACEA?
ORACEA is a tetracycline-class medicine. ORACEA is a prescription medicine used in adults to treat only pimples or bumps (papules and pustules) caused by a condition called rosacea. ORACEA does not lessen redness caused by rosacea.
ORACEA should not be used for the treatment or prevention of infections.
It is not known if ORACEA is:

- effective for use for longer than 16 weeks.
- safe for use longer than 9 months.
- safe and effective in children. ORACEA should not be used in infants and children less than 8 years of age because it may cause stained teeth in infants and children.

Who should not take ORACEA?
Do not take ORACEA if you are allergic to doxycycline or other medicines in the tetracycline-class. Ask your doctor or pharmacist for a list of these medicines if you are not sure.

What should I tell my doctor before taking ORACEA?
Before you take ORACEA tell your doctor if you:

- have kidney problems.
- have liver problems.
- have diarrhea or watery stools.
- have vision problems.
- have had surgery on your stomach (gastric surgery).
- have or had a yeast or fungal infection in your mouth or vagina.
- have any other medical condition. • are pregnant or plan to become pregnant. ORACEA may harm your unborn baby. Taking ORACEA while you are pregnant may cause serious side effects on the growth of bone and teeth of your baby. Stop taking ORACEA and call your doctor right away if you become pregnant while taking ORACEA.
- are breastfeeding or plan to breastfeed. ORACEA can pass into your breast milk and may harm your baby. Talk to your doctor about the best way to feed your baby if you take ORACEA. You and your doctor should decide if you will take ORACEA or breastfeed. You should not do both.

Tell your doctor about all of the medicines you take, including prescription and non-prescription medicines, vitamins, and herbal supplements. ORACEA and other medicines can affect each other causing serious side effects.
Especially tell your doctor if you take:

- a blood thinner medicine.
- a penicillin (antibacterial medicine).
- proton pump inhibitors or antacids that contain aluminum, calcium, or magnesium.
- products containing iron or bismuth subsalicylate.
- a medicine taken by mouth that contains isotretinoin or acitretin.
- a medicine to treat seizures, such as carbamazepineor or phenytoin.

Ask your doctor or pharmacist for a full list of these medicines, if you are not sure.
Know the medicines you take. Keep a list of your medicines and show it to your doctor and pharmacist when you get a new medicine.

How should I take ORACEA?

- Take ORACEA exactly as prescribed by your doctor. Taking more than your prescribed dose may increase your chance of side effects, including the chance that bacteria will become resistant to ORACEA.
- Take ORACEA 1 time a day in the morning on an empty stomach.
- You should take ORACEA at least one hour before or two hours after a meal.
- Take ORACEA with enough fluid to completely swallow the capsule and to lower your risk of getting irritation or ulcer in your esophagus. Your esophagus is the tube that connects your mouth to your stomach.
- If you took too much ORACEA call your doctor right away.
- Your doctor may do blood tests during treatment with ORACEA to check for side effects.

What should I avoid while taking ORACEA?
Avoid sunlight or artificial sunlight, such as a tanning booth or sunlamp. You could get severe sunburn. Use sunscreen and wear clothes that cover your skin while out in sunlight.

What are the possible side effects of ORACEA?
ORACEA may cause serious side effects, including:

- Harm to an unborn baby. See “What should I tell my doctor before taking ORACEA?”
- Permanent teeth discoloration. ORACEA may permanently turn a baby or child's teeth yellow-grey-brown during tooth development. ORACEA should not be used during tooth development. Tooth development happens in the last half of pregnancy, and from birth to 8 years of age. See “What should I tell my doctor before taking ORACEA?”
- Intestine infection (pseudomembranous colitis). Pseudomembranous colitis can happen with most antibiotics, including ORACEA. Call your doctor right away if you get diarrhea or bloody stools.
- Immune system reactions including a lupus-like syndrome, hepatitis,and inflammation of blood or lymph vessels (vasculitis). Stop taking ORACEA and tell your doctor right away if you get joint pain, fever, rash, or body weakness.
- Discoloration (hyperpigmentation). ORACEA can cause darkening of your skin, scars, teeth, gums, nails, and whites of your eyes.
- Benign intracranial hypertension, also called pseudotumor cerebri. This is a condition where there is high pressure in the fluid around the brain. This swelling may lead to vision changes and permanent vision loss. Stop taking ORACEA and tell your doctor right away if you have blurred vision, vision loss, or unusual headaches

The most common side effects of ORACEA include:

- soreness in the nose and throat
- sinus infection
- fungus infection
- flu-like symptoms
- diarrhea
- stomach (abdominal) bloating or pain
- high blood pressure (hypertension)
- change in certain blood tests

Tell your doctor if you have any side effect that bothers you or that does not go away.
These are not all the possible side effects of ORACEA. For more information, ask your doctor or pharmacist.
Call your doctor for medical advice about side effects. You may report side effects to FDA at 1-800-FDA-1088. You may also report side effects to Galderma Laboratories, L.P. at 1-866-735-4137

How should I store ORACEA?

- Store ORACEA at room temperature between 59°F to 86°F (15°C to 30°C).
- Keep ORACEA in a tightly closed container.
- Keep ORACEA inside container and out of light.

Keep ORACEA and all medicine out of the reach of children.

General information about ORACEA
Medicines are sometimes prescribed for purposes other than those listed in a Patient Information leaflet. Do not take ORACEA for a condition for which it was not prescribed. Do not give ORACEA to other people, even if they have the same symptoms you have. It may harm them.
This Patient Information leaflet summarizes the most important information about ORACEA. If you would like more information, talk with your doctor. You can also ask your doctor or pharmacist for information that is written for health professionals.

What are the ingredients in ORACEA?
Active ingredient: doxycycline
Inactive ingredients: hypromellose, iron oxide red, iron oxide yellow, methacrylic acid copolymer, polyethylene glycol, Polysorbate 80, sugar spheres, talc, titanium dioxide, and triethyl citrate.

Marketed by:
Galderma Laboratories, L.P.
Dallas, Texas 75201 USA
All trademarks are the property of their respective owners.
P55304-2

This Patient Information has been approved by the U.S. Food and Drug Administration.
Revised: April 2025

PACKAGE LABEL

NDC 0299-3822-30

ORACEA®

(doxycycine, USP)
capsules

40 mg*

*30 mg IMMEDIATE RELEASE &
10 mg DELAYED RELEASE BEADS

30 CAPSULES

RX ONLY

GALDERMA

Marketed by:
Galderma Laboratories, L.P.
Dallas, TX 75201 USA
All trademarks are the property of their respective owners.
oracea.com
P55303-1